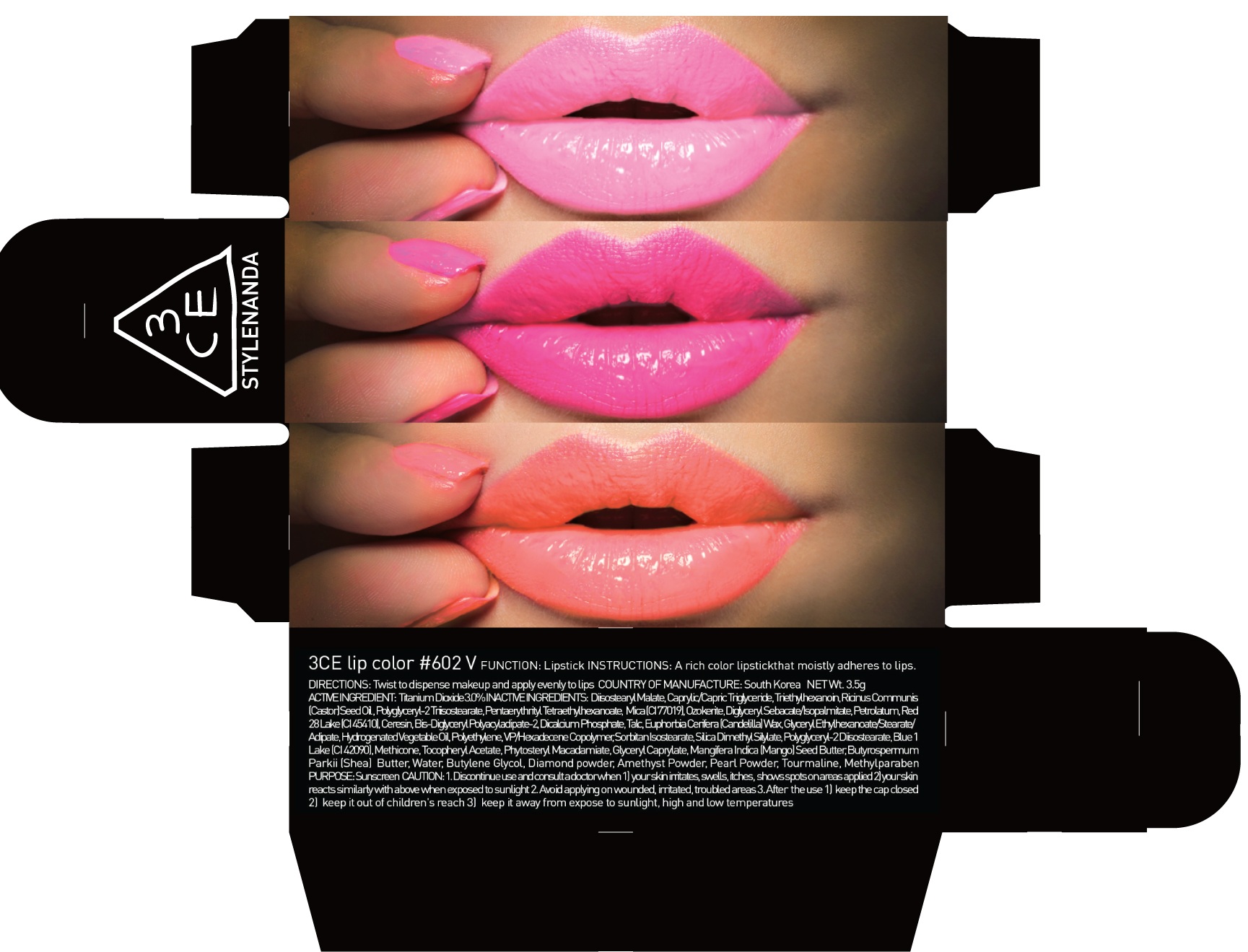 DRUG LABEL: 3CE LIP COLOR 602 V
NDC: 60764-079 | Form: LIPSTICK
Manufacturer: Nanda Co., Ltd
Category: otc | Type: HUMAN OTC DRUG LABEL
Date: 20161007

ACTIVE INGREDIENTS: Titanium Dioxide 0.10 g/3.5 g
INACTIVE INGREDIENTS: Diisostearyl Malate; Triethylhexanoin

ACTIVE INGREDIENT

Active Ingredient: Titanium Dioxide 3.0%

INACTIVE INGREDIENT

Inactive Ingredients: Diisostearyl Malate, Caprylic/Capric Triglyceride, Triethylhexanoin, RicinusCommunis (Castor) Seed Oil, Polyglyceryl-2 Triisostearate, PentaerythritylTetraethylhexanoate, Mica (CI 77019), Ozokerite, DiglycerylSebacate/Isopalmitate, Petrolatum, Red 28 Lake (CI 45410), Ceresin, Bis-Diglyceryl Polyacyladipate-2, Dicalcium Phosphate, Talc, Euphorbia Cerifera (Candelilla) Wax, Glyceryl Ethylhexanoate/Stearate/Adipate, Hydrogenated Vegetable Oil, Polyethylene, VP/Hexadecene Copolymer, SorbitanIsostearate, Silica Dimethyl Silylate, Polyglyceryl-2 Diisostearate, Blue 1 Lake (CI 42090), Methicone, Tocopheryl Acetate, PhytosterylMacadamiate, Glyceryl Caprylate, MangiferaIndica (Mango) Seed Butter, ButyrospermumParkii (Shea) Butter, Water, Butylene Glycol, Diamond powder, Amethyst Powder, Pearl Powder, Tourmaline, Methylparaben

PURPOSE

Purpose: Sunscreen

CAUTION

CAUTION: 1. Discontinue use and consult a doctor when - your skin irritates, swells, itches, shows spots on areas applied - your skin reacts similarly with above when exposed to sunlight 2. Avoid applying on wounded, irritated, troubled areas 3. After the use - keep the cap closed - keep it out of children's reach - keep it away from expose to sunlight, high and low temperatures

DESCRIPTION

INSTRUCTIONS: A rich color lipstick that moistly adheres to lips.

Directions: Twist to dispense makeup and apply evenly to lips